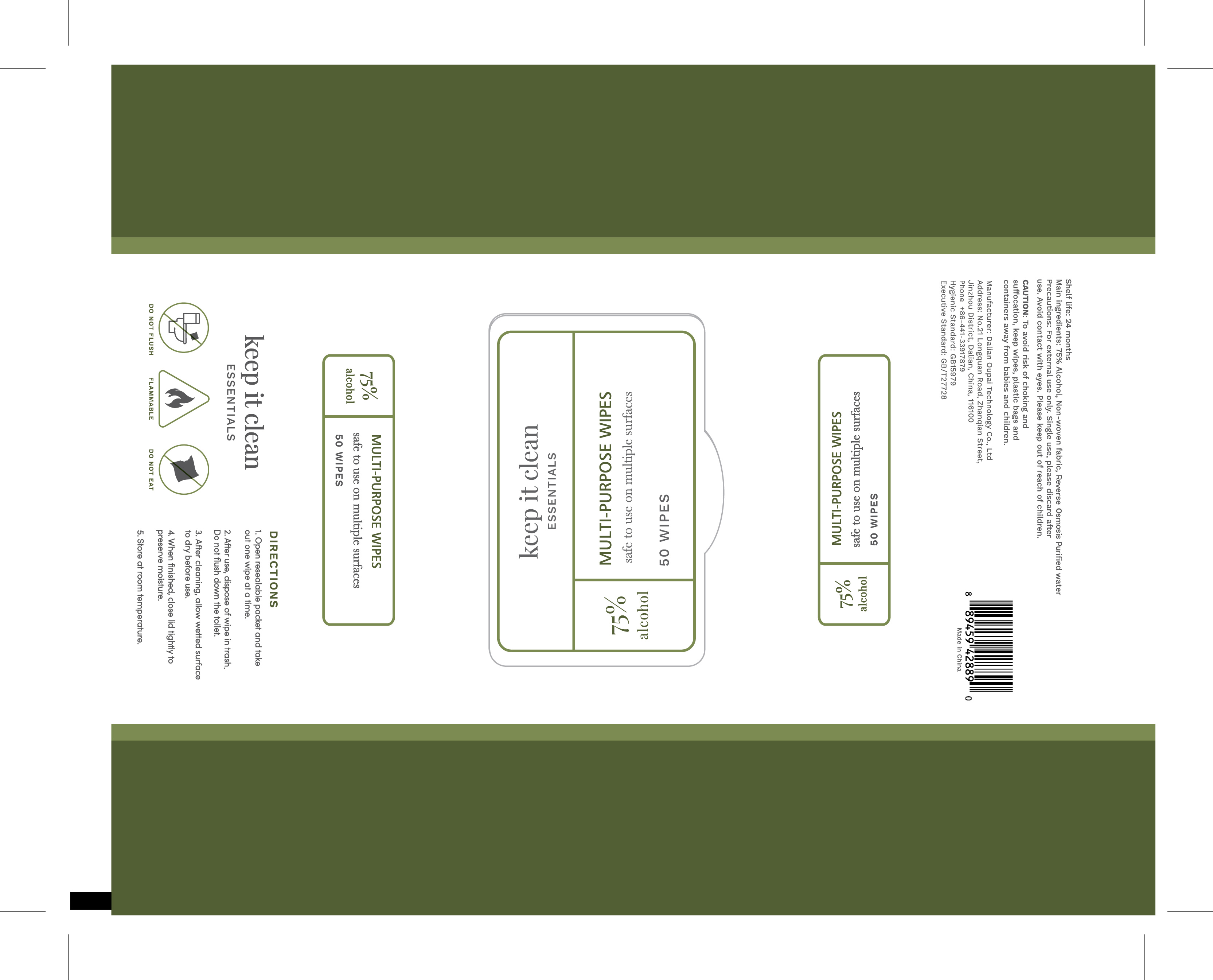 DRUG LABEL: 75% Alcohol Wipes
NDC: 78055-008 | Form: CLOTH
Manufacturer: Dalian Oupai Technology Co.,Ltd
Category: otc | Type: HUMAN OTC DRUG LABEL
Date: 20200720

ACTIVE INGREDIENTS: ALCOHOL 0.75 1/1 1
INACTIVE INGREDIENTS: WATER

Active Ingredient(s)

75% Alcohol

Purpose

wipe

Use

Hand Sanitizer to help reduce bacteria that potentially can cause disease. For use when soap and water are not available.

Warnings

To avoid risk of choking and suffocation,keep wipes,plastic bags and containers away from babies and children

When using this product keep out of eyes, ears, and mouth. In case of contact with eyes, rinse eyes thoroughly with water.
Stop use and ask a doctor if irritation or rash occurs. These may be signs of a serious condition.
Keep out of reach of children. If swallowed, get medical help or contact a Poison Control Center right away.

Stop use and ask a doctor if irritation or rash occurs. These may be signs of a serious condition.

Keep out of reach of children. If swallowed, get medical help or contact a Poison Control Center right away.

Directions

1.open resealable packet and take out one wipe at a time

2.after use,dispose of wipe in trash.do not flush down the toilet

3.after cleaning,allow wetted surface to dry before use

4.when finished,close lid tightly to preserve moisture

5.store at room temperature

Other information

- Store between 15-30C (59-86F)
- Avoid freezing and excessive heat above 40C (104F)

Inactive ingredients

non-weven fabric, reverse osmosis purified water